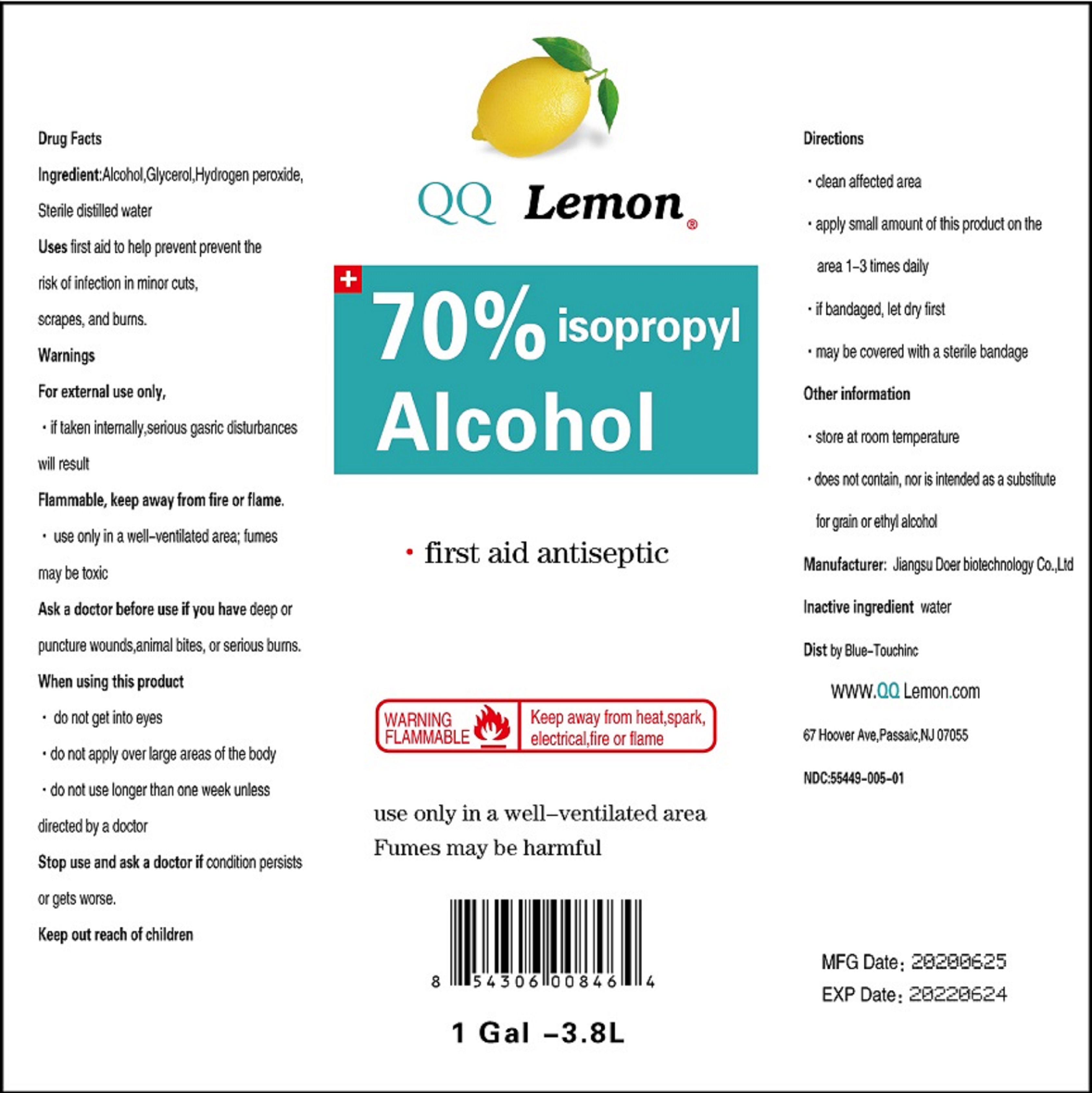 DRUG LABEL: DISINFECTANT ALCOHOL
NDC: 55449-005 | Form: LIQUID
Manufacturer: Jiangsu Doer biotechnology Co., Ltd
Category: otc | Type: HUMAN OTC DRUG LABEL
Date: 20200826

ACTIVE INGREDIENTS: ALCOHOL 70 mL/100 mL
INACTIVE INGREDIENTS: GLYCERIN; HYDROGEN PEROXIDE; WATER

55449-05-01 02 03 DISINFECTANT ALCOHOL

This is a hand sanitizer manufactured according to the Temporary Policy for Preparation of Certain Alcohol-Based Hand Sanitizer Products During the Public Health Emergency (CoViD-19); Guidance for Industry.

The hand sanitizer is manufactured using only the following United States Pharmacopoeia (USP) grade ingredients in the preparation of the product (percentage in final product formulation) consistent with World Health Organization (WHO) recommendations:

1. Alcohol (ethanol) (USP or Food Chemical Codex (FCC) grade) (80%, volume/volume (v/v)) in an aqueous solution denatured according to Alcohol and Tobacco Tax and Trade Bureau regulations in 27 CFR part 20.
2. Glycerol (1.45% v/v).
3. Hydrogen peroxide (0.125% v/v).
4. Sterile distilled water or boiled cold water.

The firm does not add other active or inactive ingredients. Different or additional ingredients may impact the quality and potency of the product.

Active Ingredient(s)

Alcohol 70% v/v. Purpose: Antiseptic

Purpose

Antiseptic, DISINFECTANT ALCOHOL

Use

fist aid to help prevent prevent the risk of infection in minor cuts, scrapes, and burms.

Do not use

- in children less than 2 months of age
- on open skin wounds

WHEN USING

- do not get into eyes.
- do not apply over large areas of the body.
- do not use longer than one week unless directed by a doctor.

Stop use and ask a doctor if condition persists or gets worse.

Keep out of reach of children. If swallowed, get medical help or contact a Poison Control Center right away.

Directions

- dean affected area
  - apply small amount of this product on the area 1-3 times daily
  - if bandaged, let dry first
  - may be covered with a sterile bandage

Other information

- store at room temperature
- does not contain, nor is intended as a substitute for grain or ethyl alcohol

Inactive ingredients

glycerin, hydrogen peroxide, purified water USP

Package Label - Principal Display Panel

NDC: 55449-005